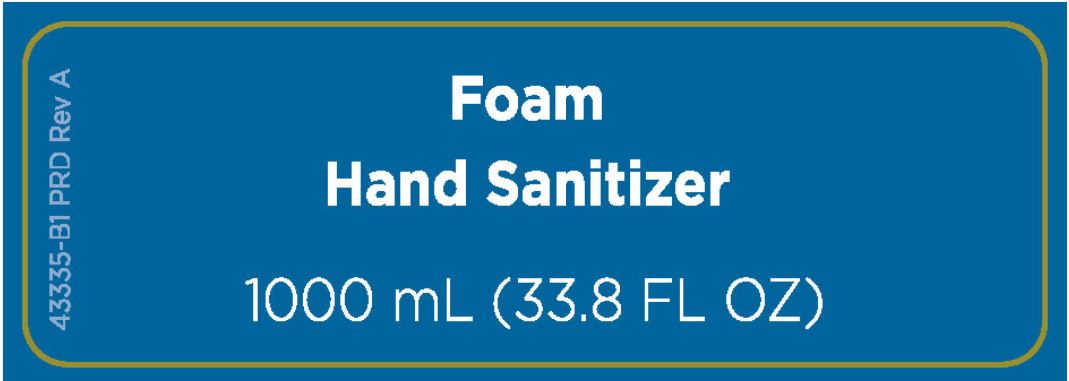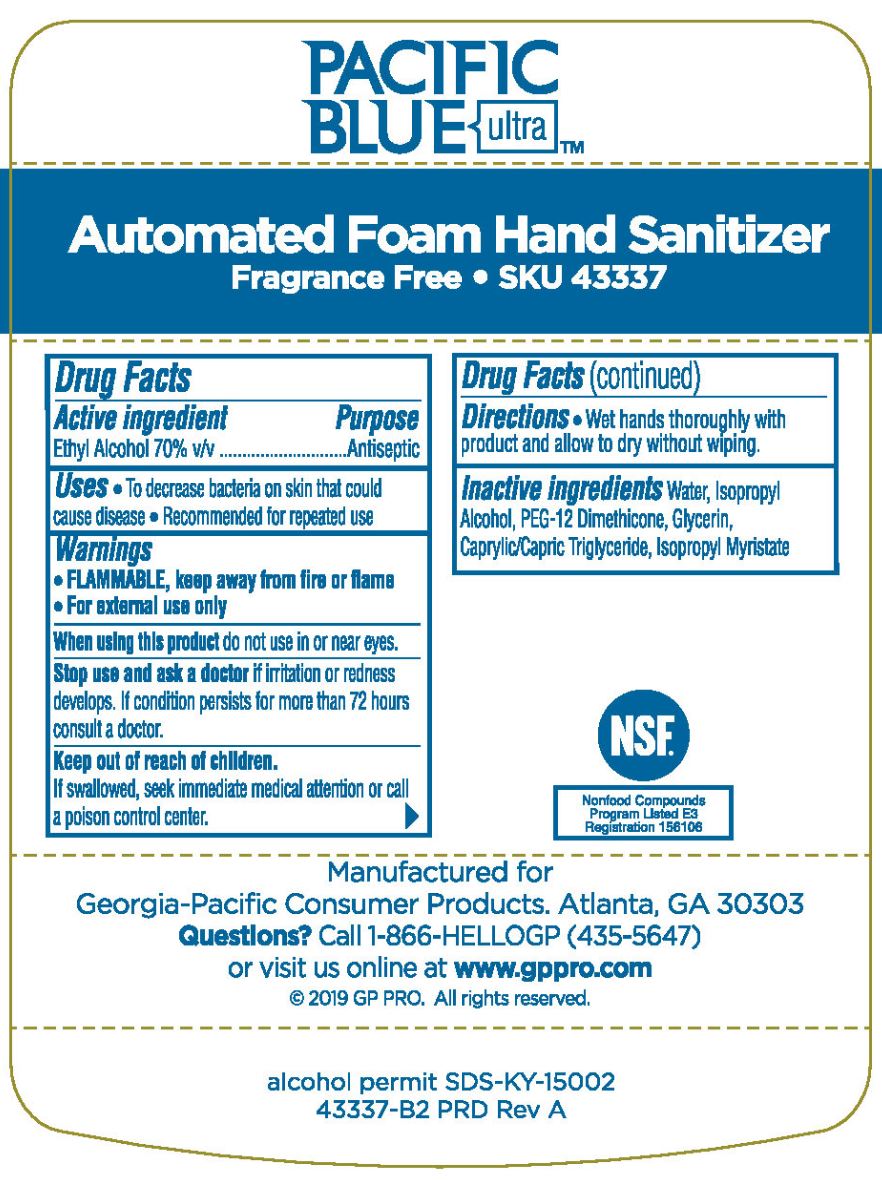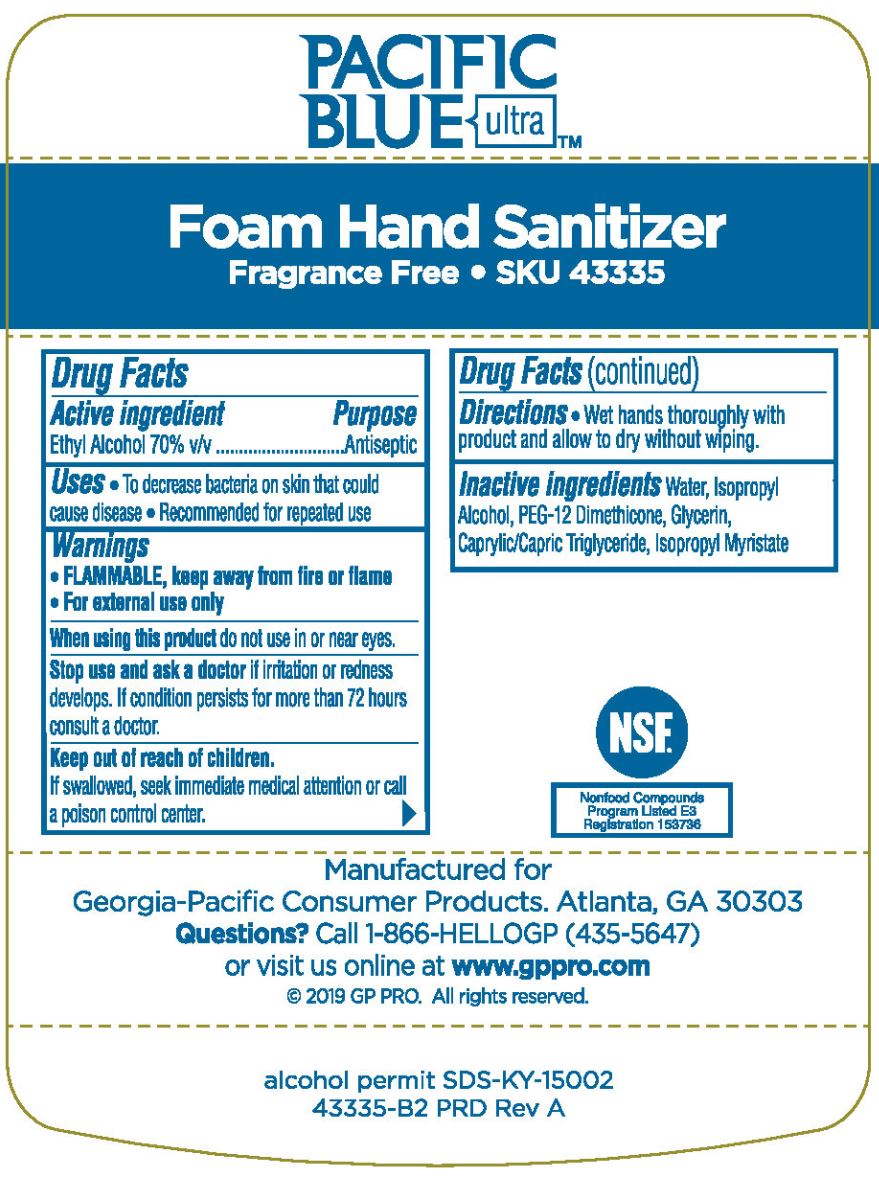 DRUG LABEL: Pacific Blue Ultra Foaming

NDC: 54622-122 | Form: SOLUTION
Manufacturer: Georgia-Pacific Consumer Products LP
Category: otc | Type: HUMAN OTC DRUG LABEL
Date: 20250123

ACTIVE INGREDIENTS: ALCOHOL 70 mg/1 mL
INACTIVE INGREDIENTS: WATER; ISOPROPYL ALCOHOL; PEG-12 DIMETHICONE; GLYCERIN; GLYCERYL CAPRYLATE/CAPRATE; ISOPROPYL MYRISTATE

Pacific Blue Ultra Foam Hand Sanitizer Fragrance Free 54622-122

Active ingredient

Ethyl Alcohol 70% v/v

Purpose

Antiseptic

Uses

- To decrease bacteria on skin that could cause disease
- Recommended for repeated use

Warnings

- FLAMMABLE, keep away from fire and flame
- For external use only

WHEN USING

When using this productdo not use in or near eyes.

Stop use and ask a doctorif irritation or redness develops.

If condition persists for more than 72 hours consult a doctor.

Keep out of reach of children.

If swallowed, seek immediate medical attention or call a poison control center.

Directions

- Wet hands thoroughly with product and allow to dry without wiping.

Inactive ingredients

Water, Isopropyl Alcohol, PEG-12 Dimethicone, Glycerin, Caprylic/Capric Triglyceride, Isopropyl Myristate

Additional rear label text

Pacific Blue Ultra

Foam Hand Sanitizer

Fragrance Free SKU 43335

Manufactured for

Georgia-Pacific Consumer Products. Atlanta, GA 30303

Quesitons?Call 1-866-HELLOGP (435-5647)

or visit us online at www.gppro.com

(c) 2019 GP PRO. All rights reserved.

alcohol permit SDS-KY-15002

43335-B2 PRD Rev A

principal display panel

Foam Hand Sanitizer

1000 mL (33.8 FL OZ)